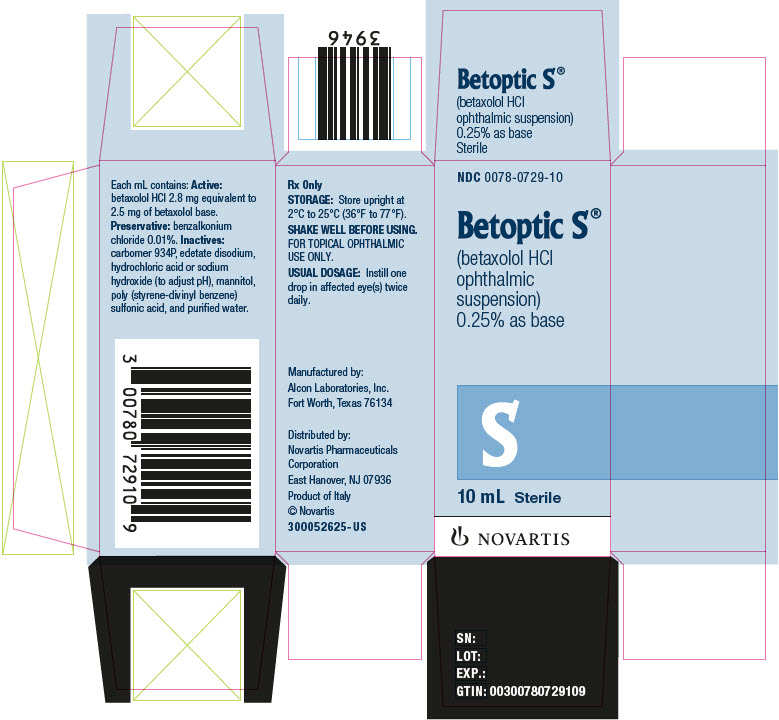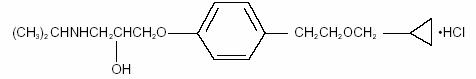 DRUG LABEL: Betoptic S
NDC: 0078-0729 | Form: SUSPENSION/ DROPS
Manufacturer: Novartis Pharmaceuticals Corporation
Category: prescription | Type: HUMAN PRESCRIPTION DRUG LABEL
Date: 20250122

ACTIVE INGREDIENTS: Betaxolol Hydrochloride 2.8 mg/1 mL
INACTIVE INGREDIENTS: Mannitol; Edetate Disodium; Hydrochloric Acid; Sodium Hydroxide; Benzalkonium Chloride; Water

HIGHLIGHTS OF PRESCRIBING INFORMATION

These highlights do not include all the information needed to use BETOPTIC S safely and effectively. See full prescribing information for BETOPTIC S.
BETOPTIC S® (betaxolol hydrochloride ophthalmic suspension), 0.25% as base, for topical ophthalmic use
Initial U.S. Approval: 1985

1 INDICATIONS AND USAGE

BETOPTIC S is a beta-adrenergic receptor inhibitor indicated for the treatment of elevated intraocular pressure (IOP) in patients with chronic open-angle glaucoma or ocular hypertension. (1)

2 DOSAGE AND ADMINISTRATION

Instill one drop in the affected eye(s) twice daily. (2)

3 DOSAGE FORMS AND STRENGTHS

Ophthalmic suspension: 2.5 mg/mL of betaxolol as base (0.25%). (3)

4 CONTRAINDICATIONS

- Hypersensitivity to any component of this product. (4)
- Sinus bradycardia, second or third degree atrioventricular (AV) block, overt cardiac failure, and cardiogenic shock. (4)

5 WARNINGS AND PRECAUTIONS

- Systemic Absorption: Same adverse reactions found with systemic administration of beta-adrenergic receptor inhibitors may occur with topical ophthalmic administration. (5.1)
- Cardiac Failure: Discontinue treatment at the first signs of cardiac failure. (5.2)
- Diabetes Mellitus: Beta-adrenergic receptor inhibitors may mask the signs and symptoms of acute hypoglycemia. Administer with caution in diabetic patients subject to hypoglycemia. (5.3)
- Thyrotoxicosis: Beta-adrenergic receptor inhibitors may mask certain clinical signs (e.g., tachycardia) or hyperthyroidism. (5.4)

6 ADVERSE REACTIONS

The most frequent adverse reaction is transient ocular discomfort. (6.1)

To report SUSPECTED ADVERSE REACTIONS, contact Novartis Pharmaceuticals Corporation at 1-888-669-6682 or FDA at 1-800-FDA-1088 or www.fda.gov/medwatch.

7 DRUG INTERACTIONS

- Oral beta-adrenergic receptor inhibitors may have additive effects. (7.1)
- Catecholamine-depleting drugs may have additive effects. (7.2)
- Concomitant adrenergic psychotropic drugs may have additive effects. (7.3)

FULL PRESCRIBING INFORMATION

1 INDICATIONS AND USAGE

BETOPTIC S® (betaxolol hydrochloride ophthalmic suspension) 0.25% is indicated for the treatment of elevated intraocular pressure (IOP) in patients with chronic open-angle glaucoma or ocular hypertension.

2 DOSAGE AND ADMINISTRATION

Instill one drop of BETOPTIC S in the affected eye(s) twice daily. Shake well before using.

BETOPTIC S may be used alone or in combination with other IOP lowering medications. Advise patients requiring concomitant topical ophthalmic medications to administer these at least 10 minutes before instilling BETOPTIC S.

3 DOSAGE FORMS AND STRENGTHS

Ophthalmic suspension containing 2.5 mg/mL of betaxolol as base (0.25%) in 10 mL and 15 mL bottles.

4 CONTRAINDICATIONS

BETOPTIC S is contraindicated in patients with:

- sinus bradycardia
- greater than a first degree atrioventricular (AV) block
- cardiogenic shock
- patients with overt cardiac failure
- hypersensitivity to any component of this product

5 WARNINGS AND PRECAUTIONS

5.1 Systemic Absorption

As with many topically applied ophthalmic drugs, this drug is absorbed systemically. The same adverse reactions found with systemic administration of beta-adrenergic receptor inhibitors may occur with topical administration. For example, severe respiratory reactions and cardiac reactions, including death due to bronchospasm in patients with asthma, and death due to cardiac failure, have been reported with topical application of beta-adrenergic receptor inhibitors.

5.2 Cardiac Failure

BETOPTIC S has been shown to have a minor effect on heart rate and blood pressure in clinical studies. Caution should be used in treating patients with a history of cardiac failure or heart block. Treatment with BETOPTIC S should be discontinued at the first signs of cardiac failure.

5.3 Diabetes Mellitus

Beta-adrenergic receptor inhibitors should be administered with caution in patients subject to hypoglycemia or to diabetic patients (especially those with labile diabetes) who are receiving insulin or oral hypoglycemic agents.

Beta-adrenergic receptor inhibitors may mask the signs and symptoms of acute hypoglycemia.

5.4 Thyrotoxicosis

Beta-adrenergic receptor inhibitors may mask certain clinical signs (e.g., tachycardia) of hyperthyroidism. Patients suspected of developing thyrotoxicosis should be managed carefully to avoid abrupt withdrawal of beta-adrenergic receptor inhibitors, which might precipitate a thyroid storm.

5.5 Muscle Weakness

Beta-adrenergic receptor inhibitors have been reported to potentiate muscle weakness consistent with certain myasthenic symptoms (e.g., diplopia, ptosis, and generalized weakness).

5.6 Surgical Anesthesia

The necessity or desirability of withdrawal of beta-adrenergic receptor inhibitors prior to major surgery is controversial. Beta-adrenergic receptor inhibitors impair the ability of the heart to respond to beta adrenergically mediated reflex stimuli. This may augment the risk of general anesthesia in surgical procedures. Some patients receiving beta-adrenergic receptor inhibitors have experienced protracted, severe hypotension during anesthesia. Difficulty in restarting and maintaining the heartbeat has also been reported. In patients undergoing elective surgery, consider gradual withdrawal of beta-adrenergic receptor inhibitors. If necessary during surgery, the effects of beta-adrenergic receptor inhibitors may be reversed by sufficient doses of adrenergic agonists.

5.7 Bronchospasm and Obstructive Pulmonary Disease

Caution should be exercised in the treatment of glaucoma patients with excessive restriction of pulmonary function. There have been reports of asthmatic attacks and pulmonary distress during betaxolol treatment. Although rechallenges of some such patients with ophthalmic betaxolol has not adversely affected pulmonary function test results, the possibility of adverse pulmonary effects in patients sensitive to beta-adrenergic receptor inhibitors cannot be ruled out.

5.8 Atopy/Anaphylaxis

While taking beta-adrenergic receptor inhibitors, patients with a history of atopy or a history of severe anaphylactic reaction to a variety of allergens may be more reactive to repeated accidental, diagnostic, or therapeutic challenge with such allergens. Such patients may be unresponsive to the usual doses of epinephrine used to treat anaphylactic reactions.

5.9 Angle-Closure Glaucoma

In patients with angle-closure glaucoma, the immediate treatment objective is to reopen the angle. This may require constricting the pupil. Betaxolol has little or no effect on the pupil and should not be used alone in the treatment of angle-closure glaucoma.

5.10 Vascular Insufficiency

Because of potential effects of beta-adrenergic receptor inhibitors on blood pressure and pulse, these inhibitors should be used with caution in patients with vascular insufficiency. If signs or symptoms suggesting reduced cerebral blood flow or Raynaud’s phenomenon develop following initiation of therapy with BETOPTIC S, alternative therapy should be considered.

5.11 Bacterial Keratitis

Bacterial keratitis may occur with use of multiple dose containers of topical ophthalmic products when these containers are inadvertently contaminated by patients who, in most cases, had a concurrent corneal disease or a disruption of the ocular epithelial surface. Instruct patients on appropriate instillation techniques [see Patient Counseling Information (17)].

5.12 Choroidal Detachment

Choroidal detachment after filtration procedures has been reported with the administration of aqueous suppressant therapy.

5.13 Contact Lens Wear

The preservative in BETOPTIC S, benzalkonium chloride, may be absorbed by soft contact lenses. Contact lenses should be removed during instillation of BETOPTIC S but may be reinserted 15 minutes after instillation [see Patient Counseling Information (17)].

6 ADVERSE REACTIONS

6.1 Clinical Trials Experience

Because clinical trials are conducted under widely varying conditions, adverse reaction rates observed in the clinical trials of a drug cannot be directly compared to rates in the clinical trials of another drug and may not reflect the rates observed in practice.

In clinical trials, the most frequent adverse reaction associated with the use of BETOPTIC S has been transient ocular discomfort. The following other adverse reactions have been reported in small numbers of patients:

Ocular: blurred vision, corneal punctate keratitis, foreign body sensation, photophobia, tearing, itching, dryness of eyes, erythema, inflammation, discharge, ocular pain, decreased visual acuity, and crusty lashes.

Systemic Adverse Reactions Include:

Cardiovascular: Bradycardia, heart block, and congestive failure.

Pulmonary: Pulmonary distress characterized by dyspnea, bronchospasm, thickened bronchial secretions, asthma, and respiratory failure.

Central Nervous System: Insomnia, dizziness, vertigo, headaches, depression, lethargy, and increase in signs, and symptoms of myasthenia gravis.

Other: Hives, toxic epidermal necrolysis, hair loss and glossitis. Perversions of taste and smell have been reported.

In a 3-month, double-masked, active-controlled, multicenter study in pediatric patients, the adverse reaction profile of BETOPTIC S was comparable to that seen in adult patients.

6.2 Additional Potential Adverse Reactions Associated With Betaxolol

Additional medical events reported with other formulations of betaxolol include allergic reactions, decreased corneal sensitivity, corneal punctate staining which may appear in dendritic formation, edema, and anisocoria.

7 DRUG INTERACTIONS

7.1 Oral Beta-Adrenergic Receptor Inhibitors

Patients who are receiving a beta-adrenergic receptor inhibitor orally and BETOPTIC S should be observed for a potential additive effect either on the IOP or on the known systemic effects of beta blockade.

7.2 Catecholamine-Depleting Drugs

Close observation of the patient is recommended when a beta-adrenergic receptor inhibitor is administered to patients receiving catecholamine-depleting drugs, such as reserpine, because of possible additive effects and the production of hypotension and/or bradycardia, which may result in vertigo, syncope, or postural hypotension.

7.3 Concomitant Adrenergic Psychotropic Drugs

Betaxolol is an adrenergic receptor inhibitor; therefore, caution should be exercised in patients using concomitant adrenergic psychotropic drugs.

7.4 Calcium Antagonists, Antiarrhythmics and Digitalis

The concomitant use of a beta-adrenergic receptor inhibitor with calcium antagonists, antiarrhythmics (including amiodarone) or digitalis may have additive effects resulting in hypotension and/or marked bradycardia.

8 USE IN SPECIFIC POPULATIONS

8.1 Pregnancy

Risk Summary

There are no adequate and well-controlled studies of BETOPTIC S administration in pregnant women to inform a drug-associated risk. There are limited data with the use of betaxolol eye drops in pregnant women. Epidemiological studies have not revealed malformative effects but show a risk for intrauterine growth retardation when beta-blockers are administered by the oral route.

In animal reproductive studies, no drug-induced maternal toxicity or teratogenicity was observed at clinically relevant doses (see Data).

Because animal reproductive studies are not always predictive of human response, BETOPTIC S should be used during pregnancy only if the potential benefit justifies the potential risk to the fetus.

In the U.S. general population, the estimated background risk of major birth defects is 2% to 4% and of miscarriage is 15% to 20% of clinically recognized pregnancies.

Data

Animal Data

In a rat embryo-fetal development (EFD) study, oral administration of 4, 40, or 400 mg/kg/day betaxolol on gestational days 6 through 18, the period of organogenesis, resulted in marked embryo-fetal lethality, increased incidence of skeletal and visceral abnormalities, and decreased fetal weights at the maternally toxic dose of 400 mg/kg/day (7785 times higher than the maximum recommended human ophthalmic dose [MRHOD] of 0.0083 mg/kg/day, on a mg/m^2 basis). The no-observed-adverse-effect-level (NOAEL) for maternal or embryo-fetal toxicity was 40 mg/kg/day (778 times higher than the MRHOD, on a mg/m^2 basis). In a rabbit EFD study, oral administration of 1, 4, 12, and 36 mg/kg/day betaxolol on gestational days 6 through 18, the period of organogenesis, resulted in a marked increase in embryo-fetal lethality at 36 mg/kg/day (1400 times higher than the MRHOD, on a mg/m^2 basis). No maternal toxicity was reported in this study.

In a perinatal and postnatal development study in rats, oral administration of 4, 32, and 256 mg/kg/day betaxolol during late gestation through lactation resulted in a marked decrease in offspring survival within 4 days postpartum at the highest dose (4982 times higher than the MRHOD, on a mg/m^2 basis). In surviving F1 offspring, growth/development and reproductive function were also affected. The NOAEL was 32 mg/kg/day (623 times higher than the MRHOD, on a mg/m^2 basis).

In a prenatal and postnatal development study in rats, an oral betaxolol dose of 150 mg/kg/day (2920 times higher than the MRHOD, on mg/m^2 basis) administered throughout the entire gestation period and lactation, resulted in maternal and developmental toxicity in F1 offspring, including decreased offspring survival, body weight and growth/development and functional deficits in surviving offspring. No NOAEL for developmental or maternal toxicity was established in this study.

Oral administration of 4, 32, and 256 mg/kg/day betoxolol to rats prior to mating and through late gestation, or until weaning, produced embryo-fetal lethality, neonatal mortality, decreased mean fetal weight, growth/development and functional deficits in surviving offspring at 256 mg/kg/day (4982 times higher than the MRHOD, on a mg/m^2 basis). At 32 mg/kg/day (623 higher than the MRHOD, on a mg/m^2 basis), decreased mean fetal weight on Gestation Day 20, and pup weight at birth and on Day 4 postpartum were observed. At 4 mg/kg/day (78 times higher than the MRHOD, on a mg/m^2 basis), a slight decrease in mean fetal weight was observed on Gestation Day 20.

8.2 Lactation

Risk Summary

Beta-blockers are excreted in breast milk following oral administration, having the potential to cause serious undesirable effects in the infant of the nursing mother. It is not known whether measurable levels of betaxolol would be present in maternal milk following topical ocular administration.

The developmental and health benefits of breastfeeding should be considered along with the mother’s clinical need for BETOPTIC S, and any potential adverse effects on the breast-fed child from BETOPTIC S.

8.4 Pediatric Use

Safety and IOP lowering effect of BETOPTIC S has been demonstrated in pediatric patients in a 3 month, multicenter, double-masked, active-controlled trial.

8.5 Geriatric Use

No overall differences in safety or effectiveness have been observed between elderly and younger patients.

10 OVERDOSAGE

No information is available on overdosage in humans. The oral LD50 of the drug ranged from 350 to 920 mg/kg in mice and 860 to 1,050 mg/kg in rats. The symptoms which might be expected with an overdose of a systemically administered beta-adrenergic receptor inhibitor are bradycardia, hypotension, bronchospasm, and acute cardiac failure.

A topical overdose of BETOPTIC S may be flushed from the eye(s) with warm tap water. If overdose occurs, treatment should be symptomatic and supportive.

11 DESCRIPTION

BETOPTIC S contains betaxolol hydrochloride, a cardioselective beta-adrenergic receptor inhibitor, in a sterile resin suspension formulation. Betaxolol hydrochloride is a white, crystalline powder, with a molecular weight of 343.89 g/mol. The chemical structure is presented below.

Empirical Formula: C18H29NO3•HCl
Chemical Name:
(±)-1-[p-[2-(cyclopropylmethoxy) ethyl]phenoxy]-3-(isopropylamino)-2-propanol hydrochloride.

Each mL of BETOPTIC S contains: Active: betaxolol HCl 2.8 mg equivalent to 2.5 mg of betaxolol base. Preservative: benzalkonium chloride 0.01%. Inactives: carbomer 934P, edetate disodium, hydrochloric acid or sodium hydroxide (to adjust pH), mannitol, poly (styrene-divinyl benzene) sulfonic acid, and purified water.

BETOPTIC S has pH of approximately 7.6 and an osmolality of approximately 290 mOsmol/kg.

12 CLINICAL PHARMACOLOGY

12.1 Mechanism of Action

Betaxolol HCl, a cardioselective (beta-1-adrenergic) receptor inhibitor, does not have significant membrane-stabilizing (local anesthetic) activity and is devoid of intrinsic sympathomimetic action. Orally administered beta-adrenergic receptor inhibitors reduce cardiac output in healthy subjects and patients with heart disease. In patients with severe impairment of myocardial function, beta-adrenergic receptor antagonists may inhibit the sympathetic stimulatory effect necessary to maintain adequate cardiac function.

When instilled in the eye, BETOPTIC S has the action of reducing elevated IOP, whether or not accompanied by glaucoma. Ophthalmic betaxolol has minimal effect on pulmonary and cardiovascular parameters.

Elevated IOP presents a major risk factor in glaucomatous field loss. The higher the level of IOP, the greater the likelihood of optic nerve damage and visual field loss. Betaxolol has the action of reducing elevated as well as normal IOP and the mechanism of ocular hypotensive action appears to be a reduction of aqueous production as demonstrated by tonography and aqueous fluorophotometry.

12.2 Pharmacodynamics

The onset of action with betaxolol can generally be noted within 30 minutes and the maximum effect can usually be detected 2 hours after topical administration. A single dose provides a 12-hour reduction in IOP. In some patients, the IOP lowering responses to BETOPTIC S may require a few weeks to stabilize. As with any new medication, careful monitoring of patients is advised.

Ophthalmic betaxolol solution at 1% (one drop in each eye) was compared to placebo in a crossover study challenging nine patients with reactive airway disease. Betaxolol HCl had no significant effect on pulmonary function as measured by forced expiratory volume in 1 second (FEV1), forced vital capacity (FVC), FEV1/FVC, and was not significantly different from placebo. The action of isoproterenol, a beta stimulant, administered at the end of the study was not inhibited by ophthalmic betaxolol.

No evidence of cardiovascular beta-adrenergic blockade during exercise was observed with betaxolol in a double-masked, crossover study in 24 normal subjects comparing ophthalmic betaxolol and placebo for effects on blood pressure and heart rate.

13 NONCLINICAL TOXICOLOGY

13.1 Carcinogenesis, Mutagenesis, Impairment of Fertility

Carcinogenesis

In 2-year carcinogenicity studies, betaxolol HCl demonstrated no carcinogenic effect at doses up to 60 mg/kg/day in mice and 48 mg/kg/day in rats (584 and 934 times higher than the MRHOD, on a mg/m^2 basis, respectively).

Mutagenesis

In a variety of in vitro and in vivo bacterial and mammalian cell assays, betaxolol HCl was not mutagenic.

Impairment of Fertility

Betaxolol did not adversely affect fertility or mating performance of male or female rats at doses up to 256 mg/kg/day (4982 times higher than the MRHOD, on a mg/m^2 basis).

14 CLINICAL STUDIES

In controlled double-masked studies, the magnitude and duration of the ocular hypotensive effect of BETOPTIC S (betaxolol hydrochloride ophthalmic suspension) 0.25% and BETOPTIC (betaxolol hydrochloride ophthalmic solution) 0.5% were clinically equivalent.

16 HOW SUPPLIED/STORAGE AND HANDLING

BETOPTIC S (betaxolol hydrochloride ophthalmic suspension), 0.25% is supplied as follows: 10 mL and 15 mL in plastic ophthalmic dispensers. Tamper evidence is provided with a shrink band around the closure and neck area of the package.

10 mL NDC 0078-0729-10

15 mL NDC 0078-0729-15

Storage and Handling

Store upright at 2°C to 25°C (36°F to 77°F).

Shake well before using.

After opening, BETOPTIC S can be used until the expiration date on the bottle.

17 PATIENT COUNSELING INFORMATION

Avoiding Contamination of the Product

Instruct patients to avoid allowing the tip of the dispensing container to contact the eye(s) or surrounding structures. Also instruct patients that ocular solutions, if handled improperly, could become contaminated by common bacteria known to cause ocular infections. Serious damage to the eye(s) and subsequent loss of vision may result from using contaminated solutions.

Intercurrent Ocular Conditions

Advise patients that if they have ocular surgery or develop an intercurrent ocular condition (e.g., trauma or infection), they should immediately seek their physician’s advice concerning the continued use of the present multi-dose container.

Concomitant Topical Ocular Therapy

Advise patients requiring concomitant topical ophthalmic medications to administer these at least 10 minutes before instilling BETOPTIC S.

Temporary Blurred Vision

Vision may be temporarily blurred following dosing with BETOPTIC S. Care should be exercised in operating machinery or driving a motor vehicle.

Contact Lens Wear

The preservative in BETOPTIC S, benzalkonium chloride, may be absorbed by soft contact lenses. Remove contact lenses during instillation of BETOPIC S. Contact lenses may be reinserted 15 minutes after instillation.

Distributed by:
Novartis Pharmaceuticals Corporation
East Hanover, New Jersey 07936

© Novartis

T2021-95

PRINCIPAL DISPLAY PANEL

NDC 0078-0729-10

Betoptic S®

(betaxolol HCI ophthalmic suspension) 0.25% as base

10 mL Sterile

NOVARTIS